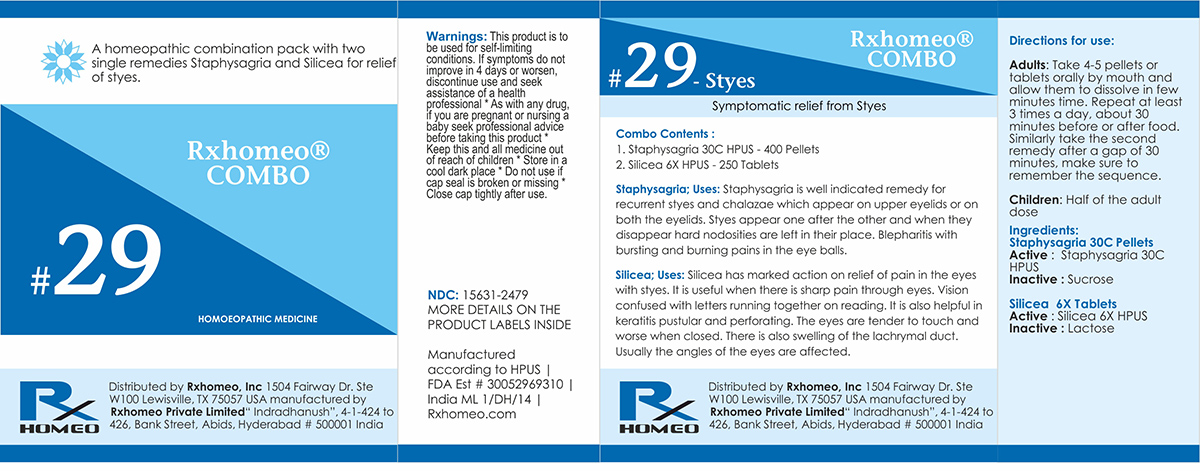 DRUG LABEL: Rxhomeo Homeopathic Combo
NDC: 15631-2479 | Form: KIT | Route: ORAL
Manufacturer: Rxhomeo Private Limited d.b.a.
Category: homeopathic | Type: HUMAN OTC DRUG LABEL
Date: 20161013

ACTIVE INGREDIENTS: DELPHINIUM STAPHISAGRIA SEED 3 [hp_X]/1 1; SILICON DIOXIDE 2 [hp_X]/1 1
INACTIVE INGREDIENTS: SUCROSE; LACTOSE

ACTIVE INGREDIENT

STAPHYSAGRIA HPUS 3X and Higher

SILICEA HPUS 2X and Higher

USES

A homeopathic combination pack with two single remedies Staphysagria and Silicea for relief of styes.

Staphysagria;Uses: Staphysagria is well indicated remedy for recurrent styes and chalazae which appear on upper eyelids or on both the eyelids. Styes appear one after the other and when they disappear hard nodosities are left in their place. Blepharitis with bursting and burning pains in the eye balls.
Silicea;Uses: Silicea has marked action on relief of pain in the eyes with styes. It is useful when there is sharp pain through eyes. Vision confused with letters running together on reading. It is also helpful in keratitis pustular and perforating. The eyes are tender to touch and worse when closed. There is also swelling of the lachrymal duct. Usually the angles of the eyes are affected.

INDICATIONS

Condition listed above or as directed by the physician

DOSAGE

PELLETS included in the Combo

Adults- Take 4 or 6 Pellets by mouth, three times daily or as suggested by physician. Children 2 years and older- take 1/2 the adult dose.

TABLETS included in the Combo

Adults- Take 4 or 6 Tablets by mouth, three times daily or as suggested by physician. Children 2 years and older- take 1/2 the adult dose.

WARNINGS

This product is to be used for self-limiting conditions

STOP USE

If symptoms do not improve in 4 days, or worsen, discontinue use and seek assistance of health professional

KEEP OUT OF REACH OF CHILDREN

Keep this and all medication out of reach of children

Do not use if capseal is broken or missing.

Close the cap tightly after use.

INACTIVE INGREDIENTS

Sucrose for Pellets.

Lactose for Tablets.

STORAGE

Store in a cool dark place

QUESTIONS OR COMMENTS

www.Rxhomeo.com | 1.888.2796642 | info@rxhomeo.com
Rxhomeo, Inc 1504 Fairway Dr. Ste W 100 Lewisville, TX 75057 USA